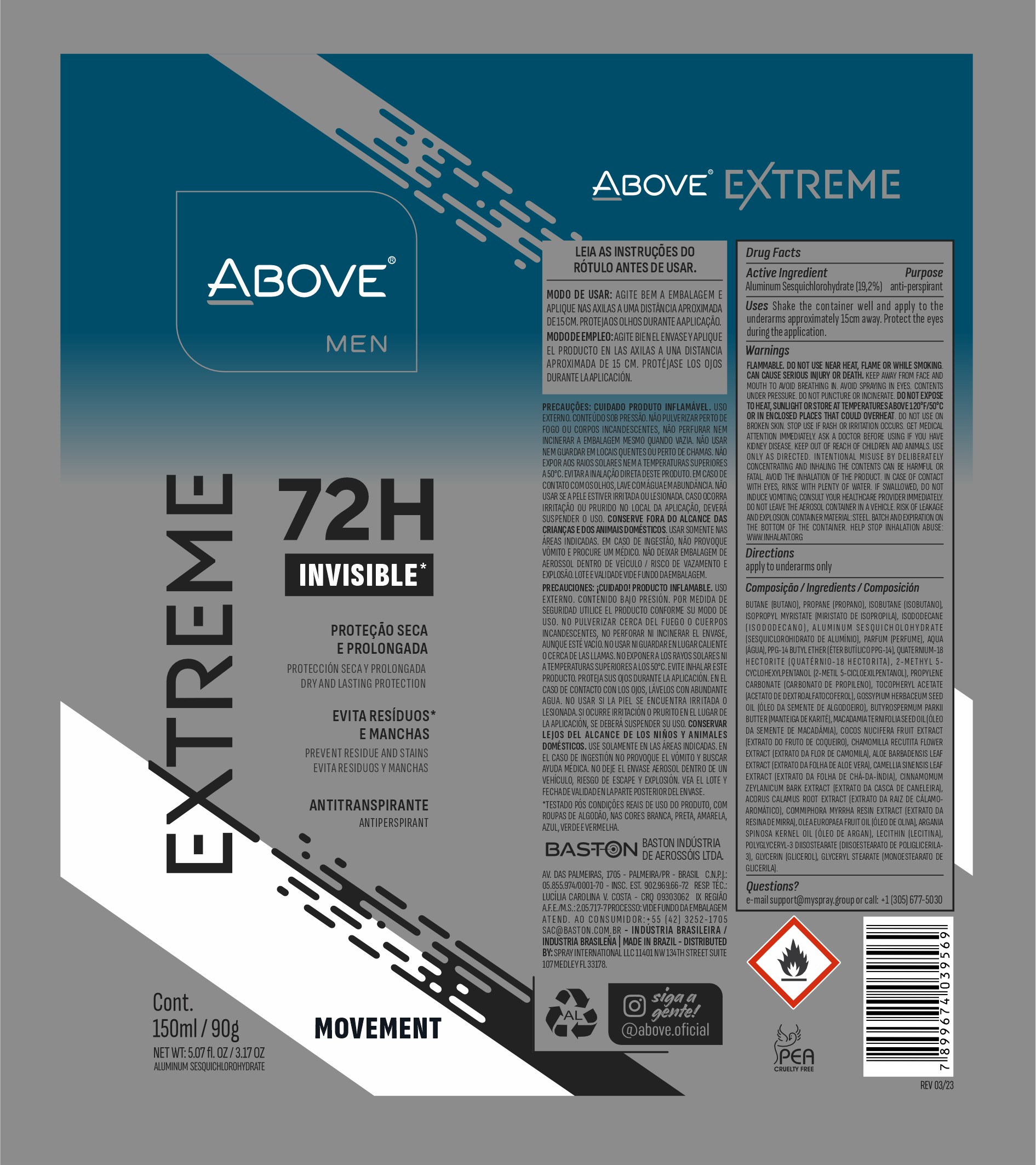 DRUG LABEL: ABOVE EXTREME MEN MOVEMENT 72 HOURS
NDC: 73306-1156 | Form: AEROSOL, SPRAY
Manufacturer: BASTON INDUSTRIA DE AEROSSOIS LTDA
Category: otc | Type: HUMAN OTC DRUG LABEL
Date: 20240709

ACTIVE INGREDIENTS: ALUMINUM SESQUICHLOROHYDRATE 19 mg/90 g
INACTIVE INGREDIENTS: ISOBUTANE

ABOVE EXTREME MEN MOVEMENT 72H SPRAY

QUESTIONS

EMAIL : SUPPORT@MYSPRAY.GROUP OR CALL (305) 677-5030